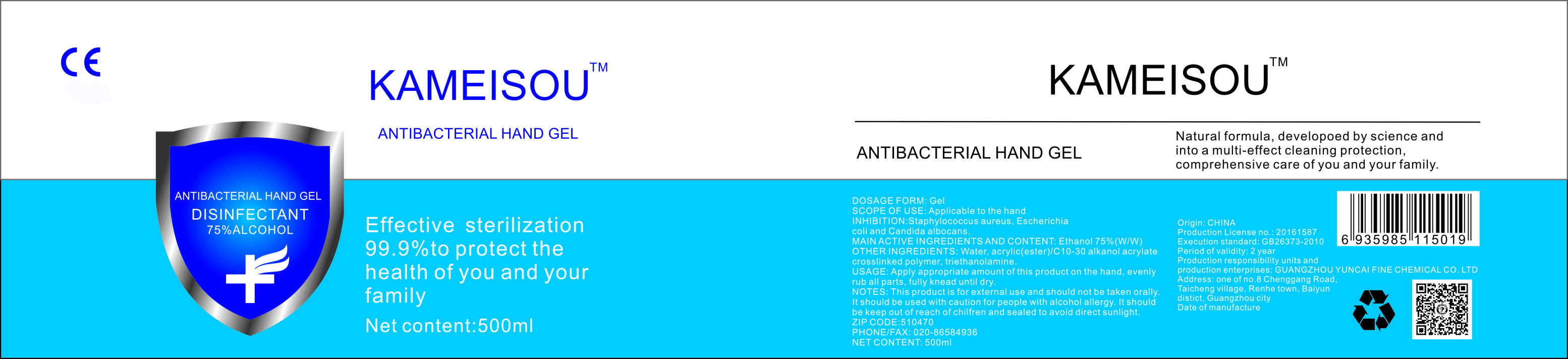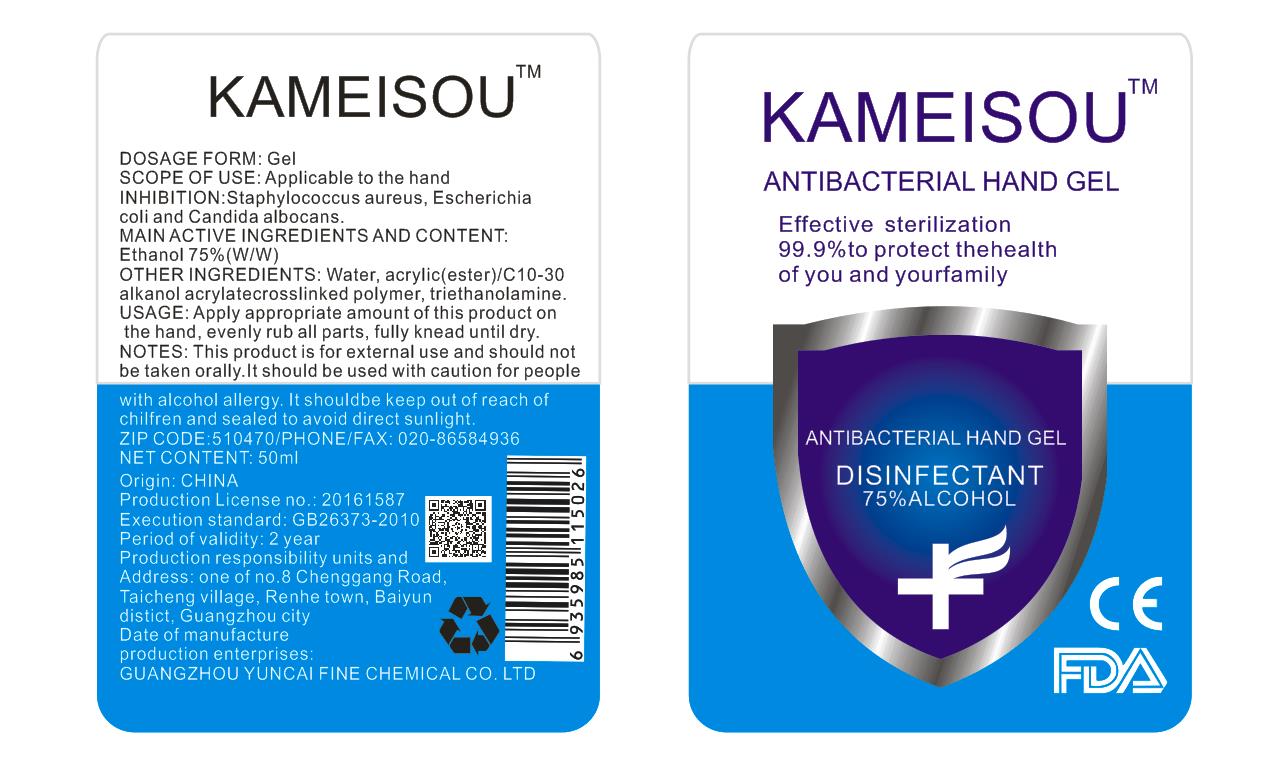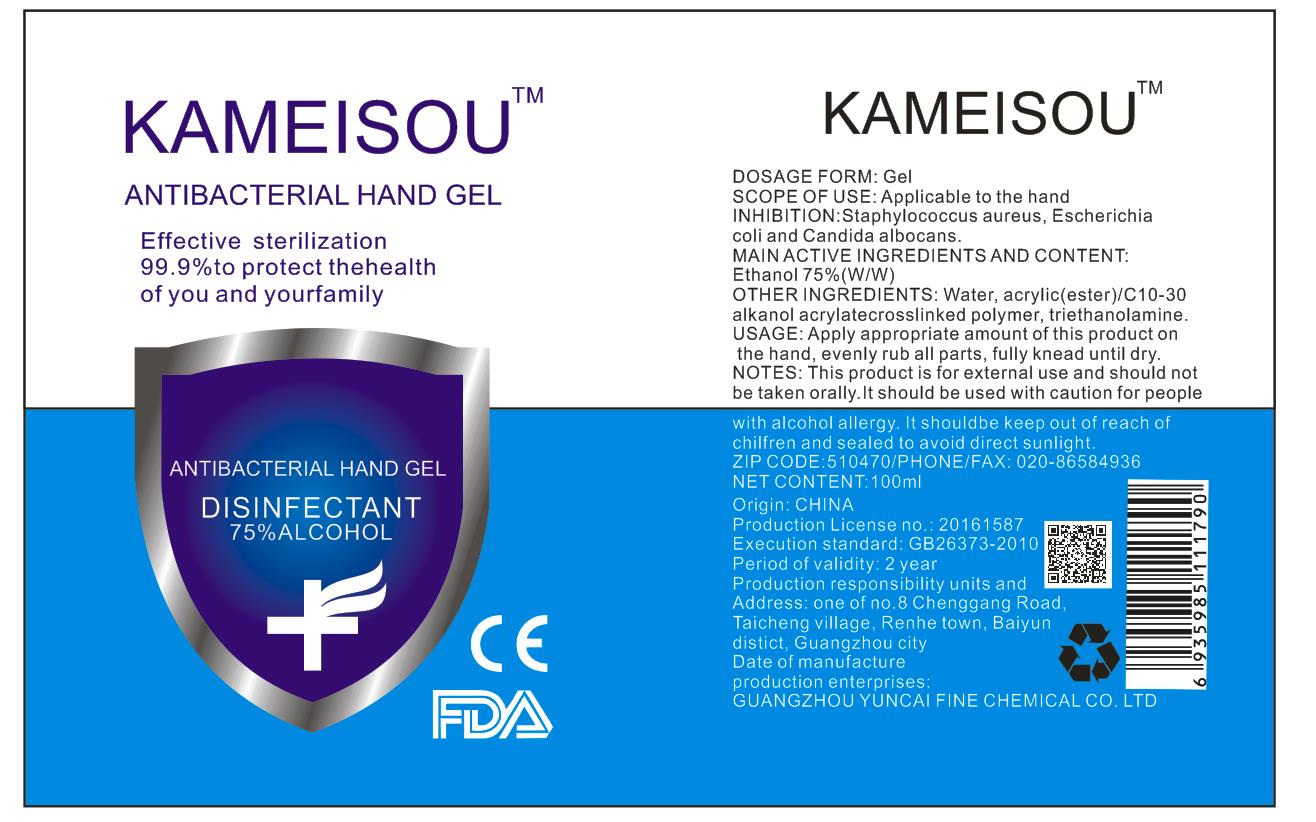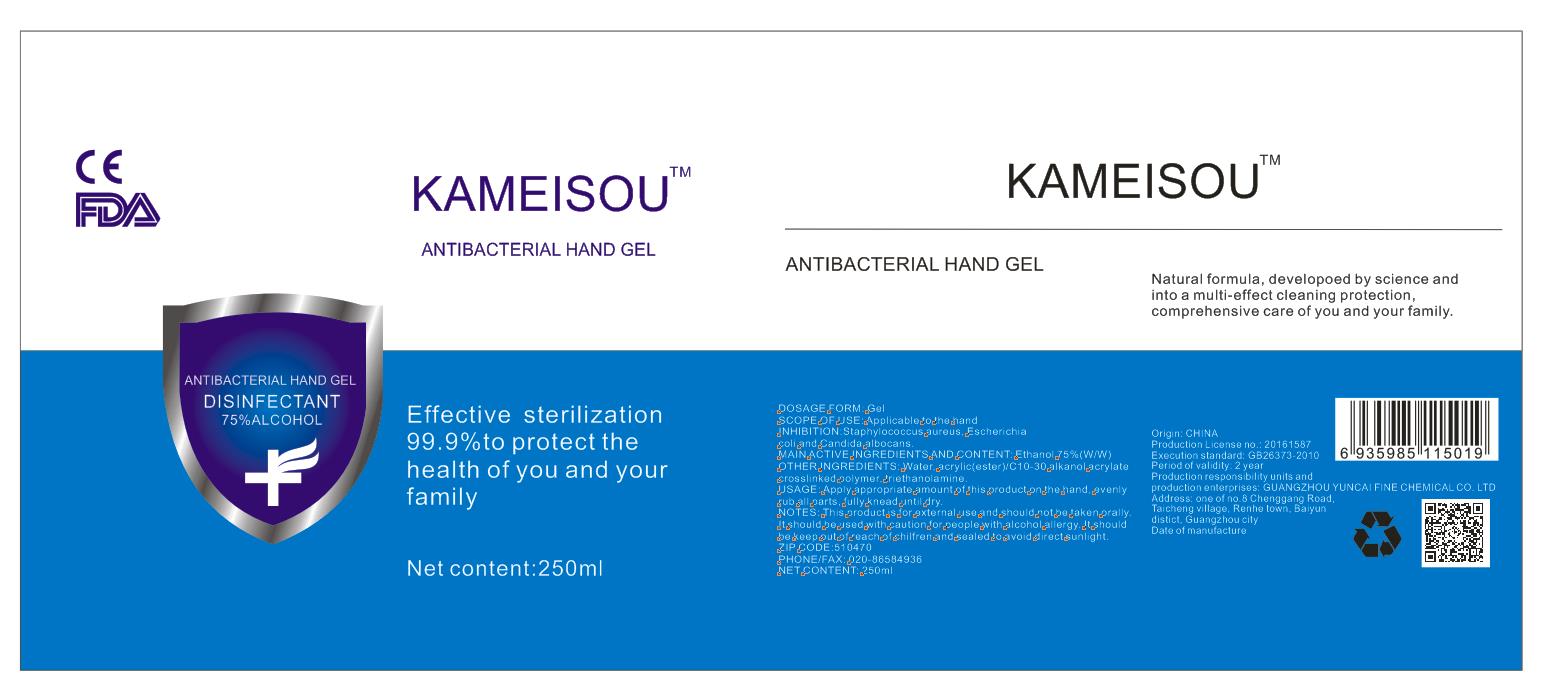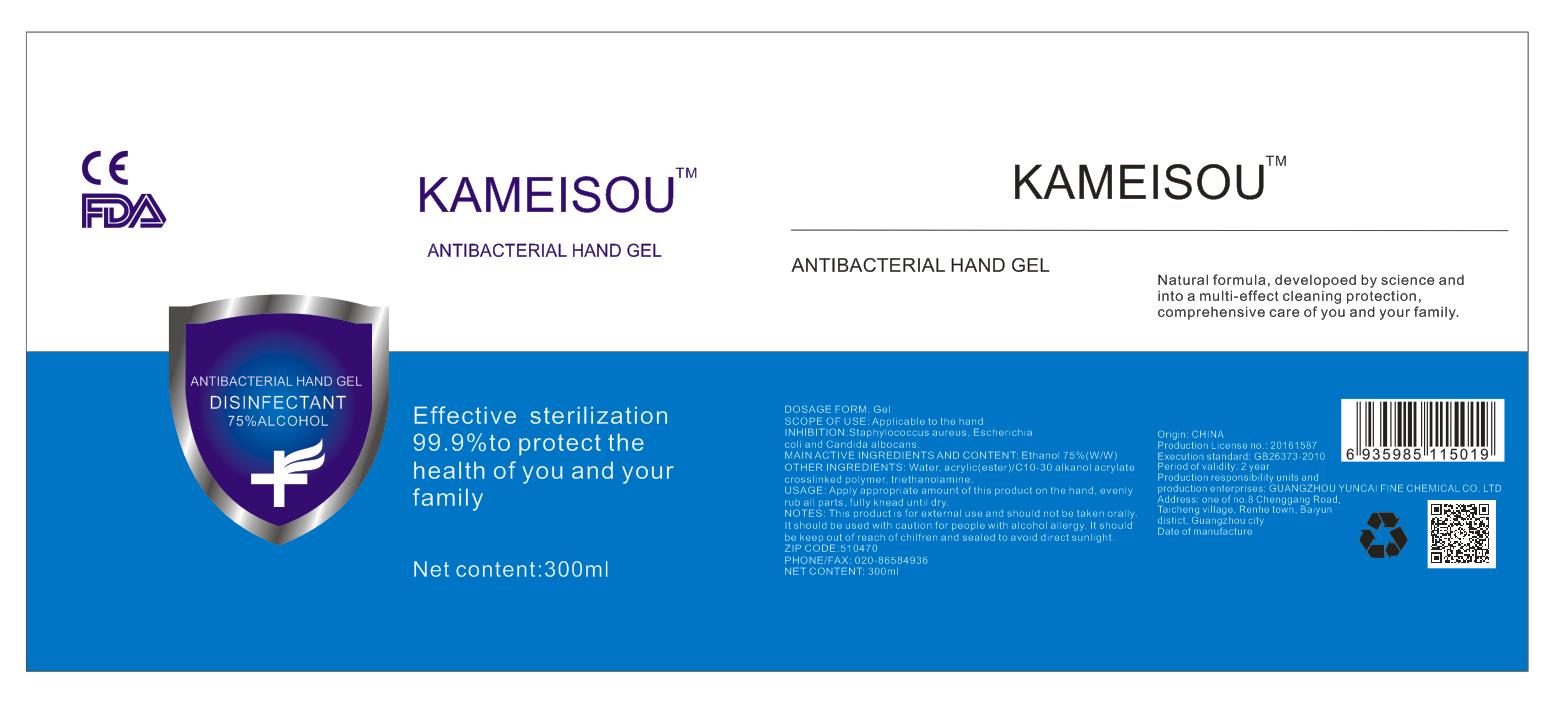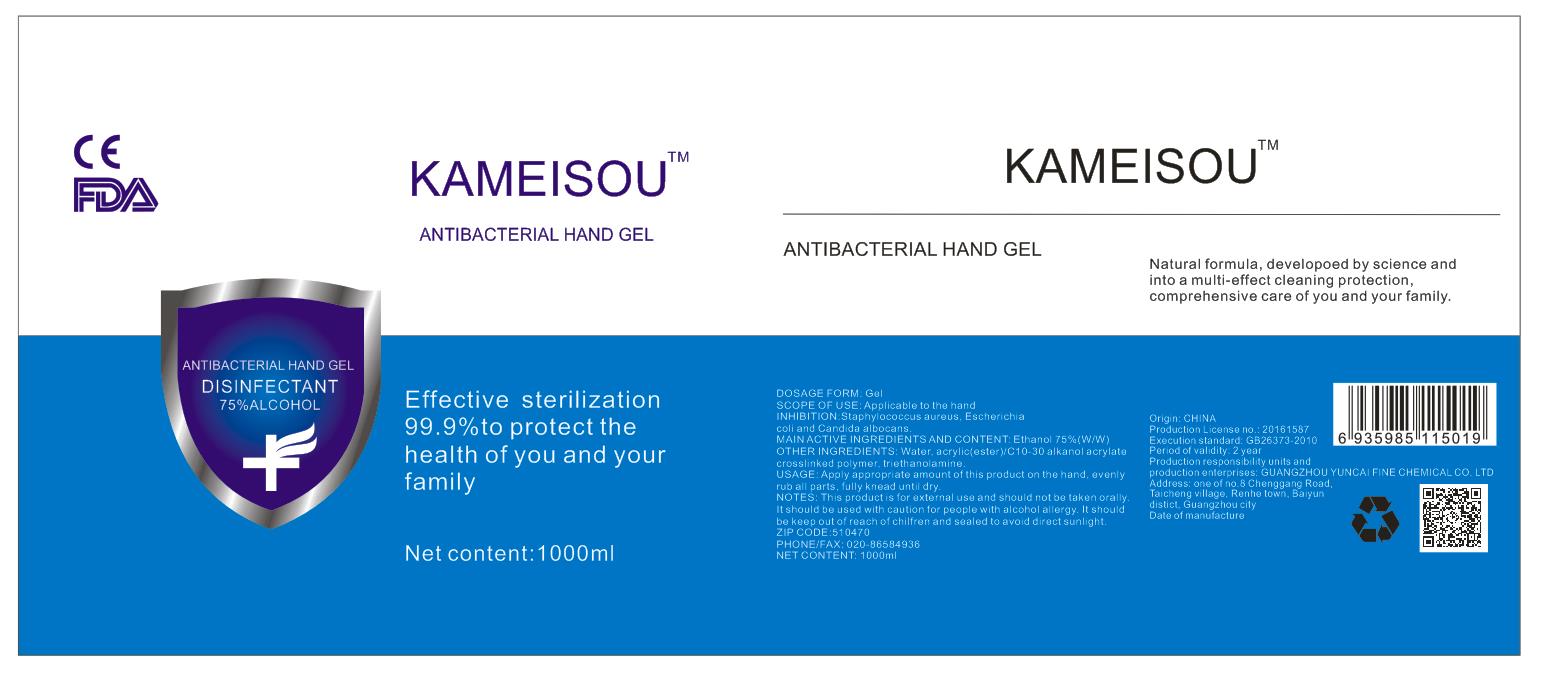 DRUG LABEL: ANTIBACTERIAL HANDS-FREE Gel
NDC: 75212-001 | Form: GEL
Manufacturer: Guangzhou Yuncai Fine Chemical CO.LTD
Category: otc | Type: HUMAN OTC DRUG LABEL
Date: 20200424

ACTIVE INGREDIENTS: ALCOHOL 75 mL/100 mL
INACTIVE INGREDIENTS: TROLAMINE; WATER

ANTIBACTERIAL HAND GEL

MAIN ACTIVE INGREDIENTS AND CONTENT

Ethanol 75%(W/W)

Use

Applicable to the hand

Directions

This product is for external use and should not be taken orally.It should be used with caution for people

with alcohol allergy.It should be keep out of reach of children and sealed to avoid direct sunlight.

Inactive ingredients

Water,acrylic(ester) /C10-30

alkanol acrylatecrosslinked polymer, triethanolamine.